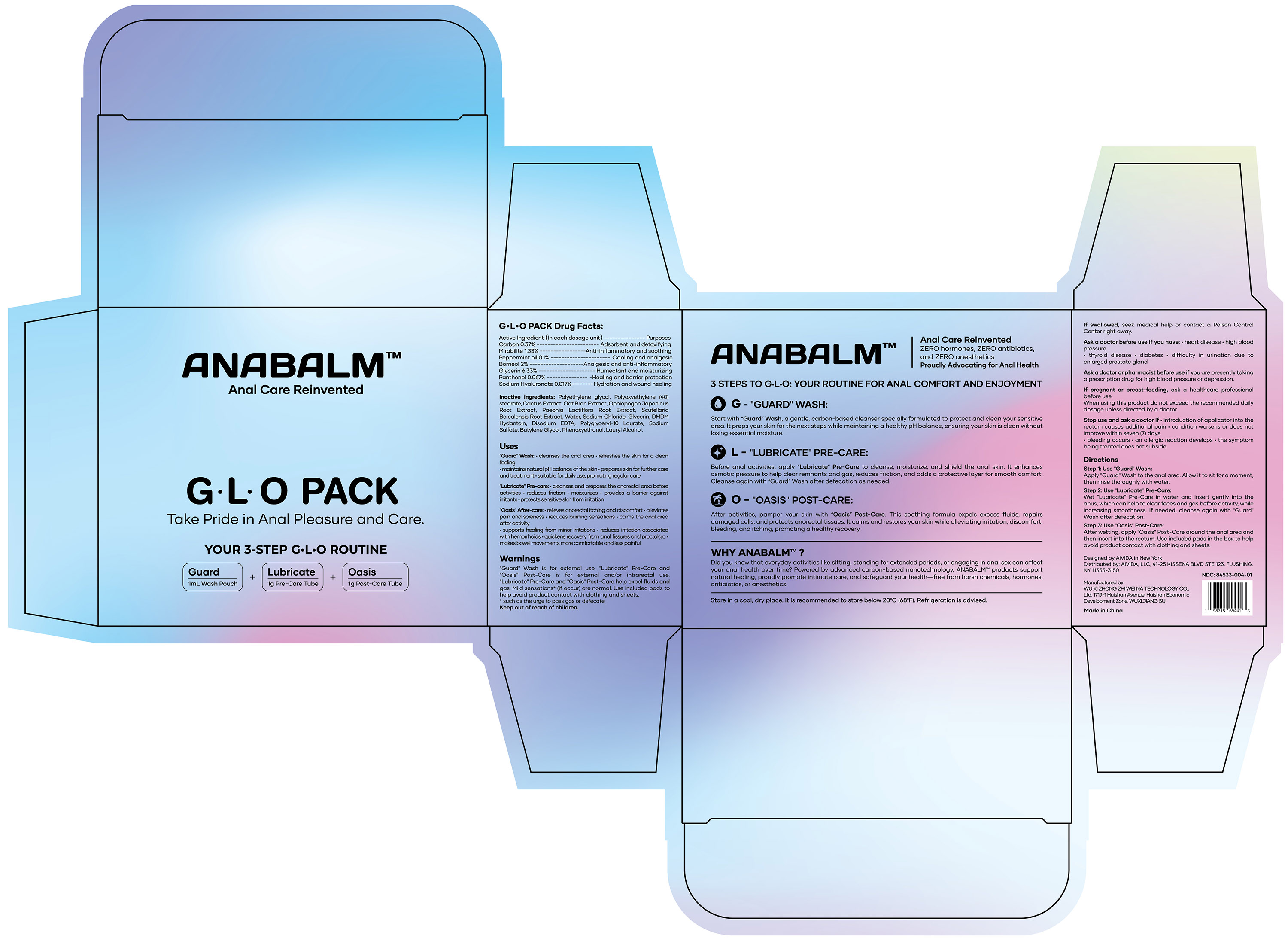 DRUG LABEL: Anal Care GLO pack
NDC: 84533-004 | Form: CREAM
Manufacturer: WU XI ZHONG ZHI WEI NA TECHNOLOGY CO., Ltd.
Category: otc | Type: HUMAN OTC DRUG LABEL
Date: 20260114

ACTIVE INGREDIENTS: SODIUM SULFATE 1.33 g/100 g; HYALURONATE SODIUM 0.017 g/100 g; PANTHENOL 0.067 g/100 g; ACTIVATED CHARCOAL 0.37 g/100 g; PEPPERMINT OIL 0.1 g/100 g; BORNEOL 2 g/100 g; GLYCERIN 6.33 g/100 g
INACTIVE INGREDIENTS: OPHIOPOGON JAPONICUS ROOT; LAURYL ALCOHOL; POLYGLYCERYL-10 LAURATE; SODIUM CHLORIDE; PHENOXYETHANOL; OPUNTIA FICUS-INDICA; PAEONIA LACTIFLORA ROOT; SCUTELLARIA BAICALENSIS ROOT; WATER; DMDM HYDANTOIN; BUTYLENE GLYCOL; POLYETHYLENE GLYCOL, UNSPECIFIED; OAT BRAN; POLYSORBATE 60; EDETATE DISODIUM

84533-004 Anal Care GLO pack

ACTIVE INGREDIENT

Carbon 0.37%
Mirabilite 1.33%
Peppermint oil 0.1%
Borneol 2%
Glycerin 6.33%
Panthenol 0.067%
Sodium Hyaluronate 0.017%

PURPOSE

Adsorbent and detoxifying, Anti-inflammatory and soothing, Cooling and analgesic, Analgesic and anti-inflammatory, Humectant and moisturizing, Healing and barrier protection, Hydration and wound healing

Keep out of reach of children.

INDICATIONS AND USAGE

"Guard" Wash: .cleanses the anal area . refreshes the skin for a cleanfeeling.maintains natural pH balance of the skin . prepares skin for further careand treatment .suitable for daily use, promoting regular care
"Lubricate" Pre-care: .cleanses and prepares the anorectal area beforeactivities .reduces friction ,moisturizes . provides a barrier againstirritants .protects sensitive skin from irritation
"Oasis" After-care: .relieves anorectal itching and discomfort . alleviatespain and soreness ,reduces burning sensations . calms the anal areaafter activity.supports healing from minor irritations .reduces irritation associatedwith hemorrhoids .quickens recovery from anal fissures and proctalgia .makes bowel movements more comfortable and less painful.

WARNINGS

"Guard" Wash is for external use. "Lubricate" Pre-Care and"Oasis" Post-Care is for external and/or intrarectal use."Lubricate" Pre-Care and "Oasis" Post-Care help expel fluids andgas. Mild sensations* (if occur) are normal. Use included pads tohelp avoid product contact with clothing and sheets.* such as the urge to pass gas or defecate.

DOSAGE AND ADMINISTRATION

Step 1: Use "Guard" Wash:Apply "Guard" Wash to the anal area. Allow it to sit for a moment,then rinse thoroughly with water.
Step 2: Use "Lubricate" Pre-Care:Wet "Lubricate" Pre-Care in water and insert gently into theanus, which can help to clear feces and gas before activity, whileincreasing smoothness. lf needed, cleanse again with "Guard"Wash after defecation.
Step 3: Use "Oasis" Post-Care:After wetting, apply "Oasis" Post-Care around the anal area andthen insert into the rectum. Use included pads in the box to helpavoid product contact with clothing and sheets.

Stop use and ask a doctor if .introduction of applicator into therectum causes additional pain .condition worsens or does notimprove within seven (7) days.bleeding occurs .an allergic reaction develops .the symptombeing treated does not subside.

STORAGE AND HANDLING

Store in a cool, dry place. lt is rec nended to store below 20'C(68°F).Refrigeration is advised.

INACTIVE INGREDIENT

Polyethylene Glycol
Polysorbate 60
Cactus Extract
Oat Bran Extract
Ophiopogon Japonicus Root Extract
Paeonia Lactiflora Root Extract
Scutellaria Baicalensis Root Extract
Water
Sodium Chloride
DMDM Hydantoin
Disodium EDTA
Polyglyceryl-10 Laurate
Sodium Sulfate
Butylene Glycol
Phenoxyethanol
Lauryl Alcohol